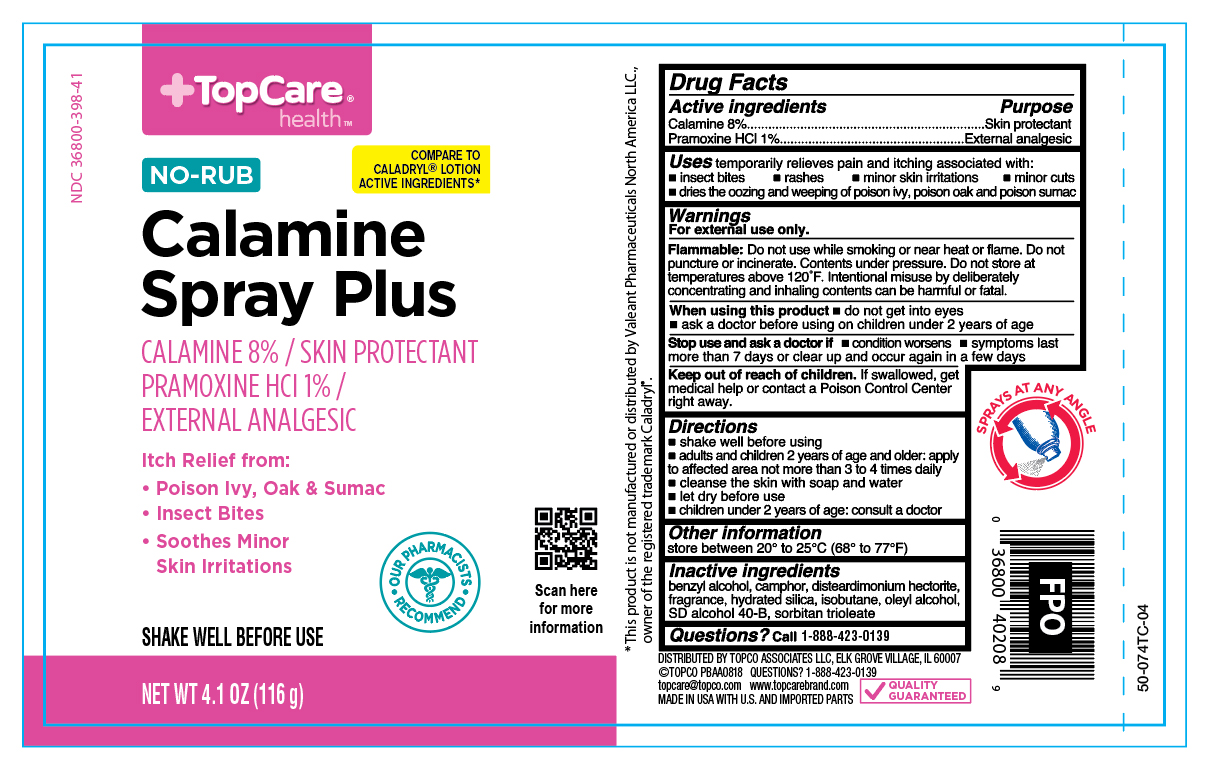 DRUG LABEL: Calamine Plus Pramoxine HCl
NDC: 36800-398 | Form: AEROSOL, SPRAY
Manufacturer: Topco Associates LLC
Category: otc | Type: HUMAN OTC DRUG LABEL
Date: 20251106

ACTIVE INGREDIENTS: FERRIC OXIDE RED 0.345 mg/116 g; ZINC OXIDE 24.16 mg/116 g; PRAMOXINE HYDROCHLORIDE 2.72 mg/116 g
INACTIVE INGREDIENTS: BENZYL ALCOHOL; CAMPHOR (SYNTHETIC); DISTEARDIMONIUM HECTORITE; HYDRATED SILICA; ISOBUTANE; OLEYL ALCOHOL; ALCOHOL; SORBITAN TRIOLEATE

TopCare Calamine Plus Spray

Active ingredient

Calamine 8%
Pramoxine HCl 1%

Purpose

Skin protectant
External analgesic

Uses

temporarily relieves pain and itching associated with:

- insect bites
- rashes
- minor skin irritations
- minor cuts
- dries the oozing and weeping of poison ivy, poison oak and poison sumac

Warnings

For external use only. Use only as directed. Intentional misuse by deliberately concentrating and inhailing contents can be harmful or fatal.

When using this product

- do not get into eyes
- ask a doctor before using on children under 2 years of age

Stop use and ask a doctor if

- conditions worsens
- symtomps last more than 7 days or clear up and occur again in a few days

Keep out of reach of children.

If swallowed, get medical help or contact a Poison Control Center right away.

Directions

- shake well before using
- adults and children 2 years of age and older: apply as needed to the affected area, not more than 3 or 4 times daily
- cleanse the skin with soap and water
- let dry before use
- children under 2 years of age: consult a doctor

Other information

store between 20° to 25°C (68° to 77°F)

Inactive ingredients

benzyl alcohol, camphor, disteardimonium hectorite, fragrance, hydrated silica, isobutane, oleyl alcohol, SD alcohol 40-B, sorbitan trioleate

Questions?

Call 1-866-964-0939

Principal Display Panel

TopCare

NO TOUCH

Calamine Plus Spray

Calamine 8% - Skin Protectant

Promoxine HCL 1% - External Analgesic

Drying action plus itch relief

Ideal for: poison ivy/oak/sumac

insect bites, minor skin irritations & cuts

SHAKE WELL BEFORE USE

NET WT 4.1 OZ (116 g)